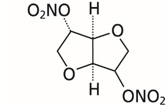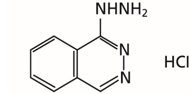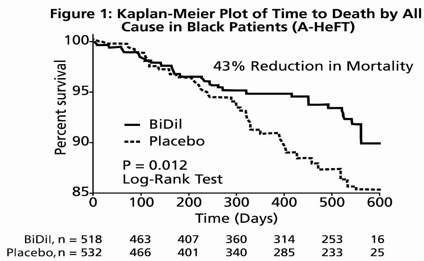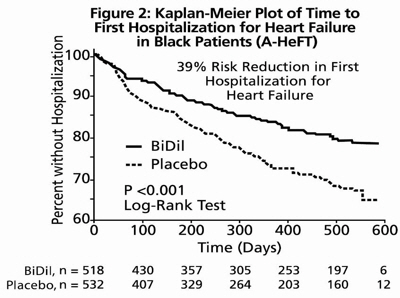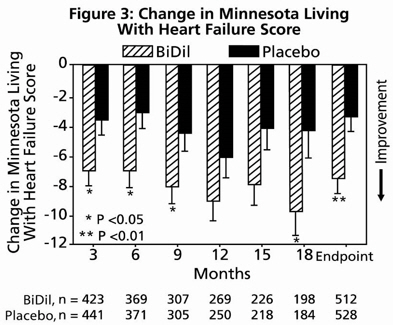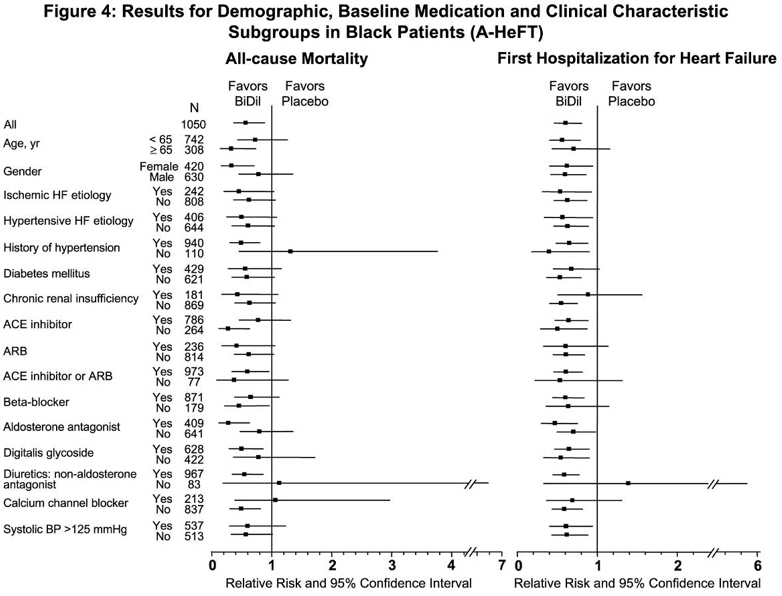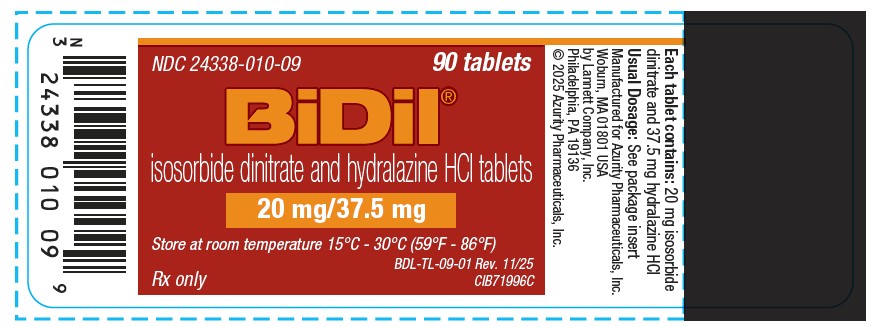 DRUG LABEL: BiDil
NDC: 24338-010 | Form: TABLET, FILM COATED
Manufacturer: Azurity Pharmaceuticals, Inc.
Category: prescription | Type: Human Prescription Drug Label
Date: 20251130

ACTIVE INGREDIENTS: Hydralazine hydrochloride 37.5 mg/1 1; Isosorbide dinitrate 20 mg/1 1
INACTIVE INGREDIENTS: anhydrous lactose; microcrystalline cellulose; sodium starch glycolate type a potato; silicon dioxide; magnesium stearate; hypromellose, unspecified; FD&C Yellow No. 6; aluminum oxide; polyethylene glycol, unspecified; titanium dioxide; polysorbate 80

HIGHLIGHTS OF PRESCRIBING INFORMATION

These highlights do not include all the information needed to use BIDIL safely and effectively. See full prescribing information for BIDIL.
BIDIL® (isosorbide dinitrate and hydralazine hydrochloride) tablet, for oral use
Initial U.S. Approval: 2005

1 INDICATIONS AND USAGE

BiDil is a combination of isosorbide dinitrate, a nitrate vasodilator, and hydralazine hydrochloride, an arteriolar vasodilator, indicated for:

- the treatment of heart failure as an adjunct therapy to standard therapy in self-identified black patients to improve survival, prolong time to hospitalization for heart failure and to improve patient-reported functional status (1.1)

Limitations of use:

- There is little experience in patients with NYHA class IV heart failure (1.2)

2 DOSAGE AND ADMINISTRATION

One tablet three times a day titrated to a maximum tolerated dose up to two tablets three times a day (2)

Dosage may be decreased to as little as one-half tablet three times a day if intolerable side effects occur. Efforts should be made to titrate up as soon as side effects subside (2)

3 DOSAGE FORMS AND STRENGTHS

Tablets (scored): 20 mg isosorbide dinitrate and 37.5 mg hydralazine hydrochloride (3)

4 CONTRAINDICATIONS

- Patients who are allergic to organic nitrates (4)
- Use of phosphodiesterase type 5 (PDE5) inhibitors, such as avanafil, sildenafil, tadalafil, or vardenafil, or soluble guanylate cyclase (sGC) stimulator (riociguat). (4)

5 WARNINGS AND PRECAUTIONS

- May cause symptomatic hypotension (5.1)
- Symptomatic Lupus Erythematosus Syndromes: Consider discontinuation if clinically appropriate (5.2)
- Myocardial ischemia and angina (5.3)
- Peripheral Neuritis: May be treated with Pyridoxine (5.4)

6 ADVERSE REACTIONS

Most common adverse reactions (≥ 5% more on BiDil than on placebo) were headache and dizziness (6.1)
To report SUSPECTED ADVERSE REACTIONS, contact Azurity Pharmaceuticals, Inc. at 1-800-461-7449 or FDA at 1-800-FDA-1088 or www.fda.gov/medwatch.

8 USE IN SPECIFIC POPULATIONS

- Geriatric Use: Isosorbide dinitrate and hydralazine may be eliminated more slowly in elderly patients. Initiate therapy at the low end of the dosing range (8.5)

FULL PRESCRIBING INFORMATION

1 INDICATIONS AND USAGE

1.1 Treatment of Heart Failure in Self-identified Black Patients

BiDil is indicated for the treatment of heart failure as an adjunct to standard therapy in self-identified black patients to improve survival, to prolong time to hospitalization for heart failure, and to improve patient-reported functional status.

1.2 Limitations of Use

There is little experience in patients with NYHA class IV heart failure.

2 DOSAGE AND ADMINISTRATION

BiDil should be initiated at a dose of one BiDil Tablet, three times a day. Titrate to a maximum of two tablets three times daily, if tolerated.

Although titration of BiDil can be rapid (3-5 days), some patients may experience side effects and may take longer to reach their maximum tolerated dose. The dosage may be decreased to as little as one-half BiDil Tablet three times a day if intolerable side effects occur. Efforts should be made to titrate up as soon as side effects subside.

3 DOSAGE FORMS AND STRENGTHS

The BiDil (20 mg isosorbide dinitrate and 37.5 mg hydralazine hydrochloride) tablets are orange, biconvex, approximately 8 mm in diameter, scored, film-coated, and debossed with "20" on one side over the score and "N" on the other side.

4 CONTRAINDICATIONS

BiDil is contraindicated in patients who are allergic to organic nitrates.

Do not use BiDil in patients who are taking PDE-5 inhibitors, such as avanafil, sildenafil, tadalafil, or vardenafil. Concomitant use can cause severe hypotension, syncope, or myocardial ischemia [see Drug Interactions (7.1)].

Do not use BiDil in patients who are taking the soluble guanylate cyclase (sGC) stimulator riociguat. Concomitant use can cause hypotension.

5 WARNINGS AND PRECAUTIONS

5.1 Hypotension

Symptomatic hypotension, particularly with upright posture, may occur with even small doses of BiDil. Hypotension is most likely to occur in patients who have been volume or salt depleted; correct prior to initiation of BiDil [see Adverse Reactions (6.1)].

5.2 Systemic Lupus Erythematosus

Hydralazine hydrochloride has been reported to cause a drug-induced systemic lupus erythematosus (SLE) syndrome. Symptoms and signs usually regress when hydralazine hydrochloride is discontinued.

5.3 Worsening Ischemic Heart Disease

Hydralazine hydrochloride can cause tachycardia and hypotension potentially leading to myocardial ischemia and angina, particularly in patients with hypertrophic cardiomyopathy.

5.4 Peripheral Neuritis

Hydralazine hydrochloride has been associated with peripheral neuritis, evidenced by paresthesia, numbness, and tingling, which may be related to an antipyridoxine effect. Pyridoxine should be added to BiDil therapy if such symptoms develop.

6 ADVERSE REACTIONS

6.1 Clinical Trials Experience

Because clinical studies are conducted under widely varying conditions, adverse reaction rates observed in the clinical studies of a drug cannot be directly compared to rates in the clinical studies of another drug and may not reflect the rates observed in practice.

BiDil has been evaluated for safety in 517 heart failure patients in A-HeFT. A total of 317 of these patients received BiDil for at least 6 months, and 220 received BiDil for at least 12 months. In A-HeFT, 21% of the patients discontinued BiDil for adverse reactions compared to 12% who discontinued placebo. Overall, adverse reactions were more common in BiDil -treated than in placebo-treated patients. Table 1 lists adverse reactions reported with an incidence, after rounding, ≥ 2% higher on BiDil than on placebo in A-HeFT, regardless of causality. The most common reasons for discontinuing BiDil in the A-HeFT trial was headache (7%).

Table 1. Adverse Reactions Occurring in the A-HeFT Study in ≥ 2% of Patients Treated with BiDil.
 | BiDil (N=517) % | Placebo (N=527) %
Headache | 50 | 21
Dizziness | 32 | 14
Asthenia | 14 | 11
Nausea | 10 | 6
Hypotension | 8 | 4
Sinusitis | 4 | 2
Ventricular tachycardia | 4 | 2
Paresthesia | 4 | 2
Vomiting | 4 | 2
Amblyopia | 3 | 1

In the V-HeFT I and II clinical studies, a total of 587 patients with heart failure were treated with the combination of isosorbide dinitrate and hydralazine hydrochloride. The type, pattern, frequency and severity of adverse reactions reported in these studies were similar to those reported in A-HeFT, described above and no unusual adverse reactions were reported.

6.2 Postmarketing Experience

The following adverse reactions have been identified during post-approval use of BiDil. Because these reactions are reported voluntarily from a population of uncertain size, it is not always possible to reliably estimate their frequency or establish a causal relationship to drug exposure.
Use of BiDil: The following adverse reactions have been identified with use of BiDil.

Cardiac Disorders: Palpitations
Ear and labyrinth disorders: Tinnitus, vertigo
Eye Disorders: Eyelid edema, vision blurred
Gastrointestinal Disorders: Abdominal discomfort, constipation
General Disorders and Administration Site Conditions: Facial pain, flushing, chest discomfort, chest pain, peripheral edema
Musculoskeletal and Connective Tissue Disorders: Pain in extremity, myalgia
Nervous Disorders: Dysgeusia, hypoaesthesia, migraine, syncope
Renal and Urinary Disorders: Chromaturia, pulmonary renal syndrome
Respiratory, Thoracic and Mediastinal Disorders: Dyspnea
Reproductive System and Breast Disorders: Erectile dysfunction
Skin and Subcutaneous Tissue Disorders: Erythema, hyperhidrosis, pruritus, face swelling

Use of Hydralazine Hydrochloride or Isosorbide Dinitrate: The following reactions have been reported with use of either hydralazine hydrochloride or isosorbide dinitrate.

Blood and Lymphatic System Disorders: Blood dyscrasias, agranulocytosis, purpura, eosinophilia, splenomegaly.
Eye Disorders: Lacrimation, conjunctivitis.
Gastrointestinal Disorders: Paralytic ileus.
Hepatobiliary Disorders: Hepatitis.
Psychiatric Disorders: Psychotic reactions, disorientation.
Renal and Urinary Disorders: Difficulty in urination.

7 DRUG INTERACTIONS

7.1 Phosphodiesterase Inhibitors

BiDil is contraindicated in patients who are using a selective inhibitor of cyclic guanosine monophosphate (cGMP)-specific phosphodiesterase type 5 (PDE5), PDE5 inhibitors such as avanafil, sildenafil, vardenafil, and tadalafil have been shown to potentiate the hypotensive effects of organic nitrates. Do not use BiDil in patients who are taking the soluble guanylate cyclase (sGC) stimulator riociguat. Concomitant use can cause hypotension [see Contraindications (4)].

8 USE IN SPECIFIC POPULATIONS

8.1 Pregnancy

Risk Summary
There are no data on BiDil use in pregnant women, and insufficient data on its components (hydralazine and isosorbide dinitrate) to assess a drug-associated risk of major birth defects or miscarriage with first trimester use. Available published data on hydralazine use in pregnancy during the second and third trimesters have not shown an association with adverse pregnancy-related outcomes.
Hydralazine hydrochloride is teratogenic in mice at 66 mg/kg and possibly in rabbits at 33 mg/kg (2 and 3 times the MRHD of BiDil on a body surface area basis).
Isosorbide dinitrate has been shown to cause a dose-related increase in embryo-toxicity (excess mummified pups) in rabbits at 70 mg/kg (12 times the MRHD of BiDil on a body surface area basis).
All pregnancies have a background risk of birth defect, loss, or other adverse outcomes. In the U.S. general population, the estimated background risk of major birth defects and miscarriage in clinically recognized pregnancies is 2-4% and 15-20%, respectively.
Clinical Considerations
Disease-Associated Maternal and/or Embryo/Fetal Risk
Pregnant women with heart failure are at increased risk for preterm birth. Clinical classification of heart disease may worsen with pregnancy and lead to maternal death and/or stillbirth.

8.2 Lactation

Risk Summary
There are no data on the presence of BIDIL in human or animal milk, the effects on the breastfed infant or on milk production. The developmental and health benefits of breastfeeding should be considered along with the mother’s clinical need for BIDIL and any potential adverse effects on the breastfed child from BIDIL or from the underlying maternal condition.

8.4 Pediatric Use

The safety and effectiveness of BiDil in children have not been established.

8.5 Geriatric Use

Clinical studies of BiDil did not include sufficient numbers of subjects aged 65 and over to determine whether they respond differently from younger subjects. Other reported clinical experience has not identified differences in response between elderly and younger patients. In general, dose selection for an elderly patient should start at the low end of the dosing range, reflecting the greater frequency of decreased hepatic and renal function, and of concomitant disease or other drug therapies.

Isosorbide dinitrate, its active metabolites, and hydralazine may be eliminated more slowly in elderly patients.

8.6 Renal Impairment

There are no studies of renal impairment using BiDil. No dose adjustment is required for hydralazine or isosorbide dinitrite [see Clinical Pharmacology (12.3)].

Dialyzability of hydralazine has not been determined. Dialysis is not an effective method for removing isosorbide dinitrate or its metabolite isosorbide-5-mononitrate from the body.

8.7 Hepatic Impairment

The effect of hepatic impairment on the pharmacokinetics of hydralazine alone has not been determined.Isosorbide dinitrate concentrations increase in patients with cirrhosis. There are no studies of hepatic impairment using BiDil.

10 OVERDOSAGE

The signs and symptoms of overdosage with BiDil are expected to be those of excessive pharmacologic effect, i.e., vasodilatation, reduced cardiac output and hypotension, and signs and symptoms include headache, confusion, tachycardia, and generalized skin flushing. Complications can include myocardial ischemia and subsequent myocardial infarction, cardiac arrhythmia, and profound shock. Syncope, coma and death may ensue without appropriate treatment.
Human Experience: There are no documented cases of overdosage with BiDil. No deaths from acute poisoning have been reported.
Treatment: There is no specific antidote. Support of the cardiovascular system is of primary importance. Shock should be treated with plasma expanders, vasopressors, and positive inotropic agents. The gastric contents should be evacuated, taking adequate precautions to prevent aspiration. These manipulations have to be carried out after cardiovascular status has been stabilized, since they might precipitate cardiac arrhythmias or increase the depth of shock.
In patients with renal disease or congestive heart failure, therapy resulting in central volume expansion is not without hazard. Treatment of isosorbide dinitrate overdose in these patients may be difficult, and invasive monitoring may be required.
No data are available to suggest physiological maneuvers (e.g., maneuvers to change the pH of the urine) that might accelerate elimination of the components of BiDil. Dialysis is not effective in removing circulating isosorbide dinitrate. The dialyzability of hydralazine has not been determined.
Methemoglobinemia: Nitrate ions liberated during metabolism of isosorbide dinitrate can oxidize hemoglobin into methemoglobin. There are case reports of significant methemoglobinemia in association with moderate overdoses of organic nitrates. Methemoglobin levels are measurable by most clinical laboratories. Methemoglobinemia could be serious in chronic heart failure patients because of already compromised vascular bed-tissue gas exchange dynamics. Classically, methemoglobinemic blood is described as chocolate brown, without color change on exposure to air. When methemoglobinemia is diagnosed, the treatment of choice is methylene blue, 1 to 2 mg/kg intravenously.

11 DESCRIPTION

BiDil is a fixed-dose combination of isosorbide dinitrate, a vasodilator with effects on both arteries and veins, and hydralazine hydrochloride, a predominantly arterial vasodilator.

Isosorbide dinitrate is described chemically as 1,4:3,6-dianhydro-D-glucitol dinitrate and its structural formula is:

Isosorbide dinitrate is a white to off-white, crystalline powder with the empirical formula C6H8N2O8 and a molecular weight of 236.14. It is freely soluble in organic solvents such as alcohol, chloroform and ether, but is only sparingly soluble in water.

Hydralazine hydrochloride is described chemically as 1-hydrazinophthalazine monohydrochloride, and its structural formula is:

Hydralazine hydrochloride is a white to off-white, crystalline powder with the empirical formula C8H8N4∙HCl and a molecular weight of 196.64. It is soluble in water, slightly soluble in alcohol, and very slightly soluble in ether.

Each BiDil Tablet for oral administration contains 20 mg of isosorbide dinitrate and 37.5 mg of hydralazine hydrochloride.

The inactive ingredients in BiDil tablets include: anhydrous lactose, microcrystalline cellulose, sodium starch glycolate, colloidal silicon dioxide, magnesium stearate, hypromellose, FD&C Yellow No. 6 aluminum lake, polyethylene glycol, titanium dioxide, polysorbate 80.

12 CLINICAL PHARMACOLOGY

12.1 Mechanism of Action

The mechanism of action underlying the beneficial effects of BiDil in the treatment of heart failure has not been established.

Isosorbide dinitrate is a vasodilator affecting both arteries and veins. Its dilator properties result from the release of nitric oxide and the subsequent activation of guanylyl cyclase, and ultimate relaxation of vascular smooth muscle.

Several well-controlled clinical trials have used exercise testing to assess the anti-anginal efficacy of chronically-delivered nitrates. In the large majority of these trials, active agents were no more effective than placebo after 24 hours (or less) of continuous therapy. Attempts to overcome nitrate tolerance by dose escalation, even to doses far in excess of those used acutely, have consistently failed. Only after nitrates have been absent from the body for several hours is response to nitrates restored.

Hydralazine hydrochloride is a selective dilator of arterial smooth muscle. Animal data suggests that hydralazine may also mitigate tolerance to nitrates.

12.2 Pharmacodynamics

The basis for the beneficial clinical effects of BiDil is not known. In a small study of patients with chronic heart failure administered single doses of hydralazine 75 mg, isosorbide dinitrate 20 mg, and the combination, the combination elicited a statistically significant decrease in pulmonary capillary wedge pressure compared to hydralazine alone. The increase in cardiac output, renal blood flow and limb blood flow with the combination, however, was not greater than with hydralazine alone. There is no study of hemodynamic effects following multiple dosing.

12.3 Pharmacokinetics

Absorption
BiDil: Following a single 75-mg oral dose of hydralazine plus 40 mg of isosorbide dinitrate to 19 healthy adults, peak plasma concentrations of hydralazine (88 ng/mL/65 kg) and isosorbide dinitrate (76 ng/mL/65 kg) were reached in 1 hour. The half-lives were about 4 hours for hydralazine and about 2 hours for isosorbide dinitrate. Peak plasma concentrations of the two active metabolites, isosorbide-2-mononitrate and isosorbide-5-mononitrate, were 98 and 364 ng/mL/65 kg, respectively, at about 2 hours. No information is currently available regarding the effect of food on the bioavailability of hydralazine or isosorbide dinitrate from BiDil tablets.
Hydralazine hydrochloride: About 2/3 of a 50-mg dose of ^14C-hydralazine hydrochloride given in gelatin capsules was absorbed in hypertensive subjects. In patients with heart failure, mean absolute bioavailability of a single oral dose of hydralazine 75 mg varies from 10 to 26%, with the higher percentages in slow acetylators. Administration of doses escalating from 75 mg to 1000 mg three times daily to congestive heart failure patients resulted in an up to 9-fold increase in the dose normalized AUC, indicating non-linear kinetics of hydralazine, probably reflecting saturable first pass metabolism.
Isosorbide dinitrate: Absorption of isosorbide dinitrate from tablets after oral dosing is nearly complete. The average bioavailability of isosorbide dinitrate is about 25%, but is highly variable (10%-90%) because of first-pass metabolism, and increases progressively during chronic therapy. Serum concentrations reach their maximum about one hour after ingestion.
Distribution
Hydralazine hydrochloride: After intravenous administration of hydralazine in a dose of 0.3 mg/kg, the steady-state volume of distribution in patients with congestive heart failure was 2.2 L/kg.
Isosorbide dinitrate: The volume of distribution of isosorbide dinitrate is 2 to 4 L/kg. About 28% of circulating isosorbide dinitrate is protein bound.
Under steady-state conditions, isosorbide dinitrate accumulates significantly in muscle (pectoral) and vein (saphenous) wall relative to simultaneous plasma concentrations.
Metabolism
Hydralazine is metabolized by acetylation, ring oxidation and conjugation with endogenous compounds including pyruvic acid. Acetylation occurs predominantly during the first-pass after oral administration which explains the dependence of the absolute bioavailability on the acetylator phenotype. About 50% of patients are fast acetylators and have lower exposure.
After oral administration of hydralazine, the major circulating metabolites are hydralazine pyruvate hydrazone and methyltriazolophthalazine. Hydralazine is the main pharmacologically active entity; hydralazine pyruvate hydrazone has only minimal hypotensive and tachycardic activity. The pharmacological activity of methyltriazolophthalazine has not been determined. The major identified metabolite of hydralazine excreted in urine is acetylhydrazinophthalazinone.
Isosorbide dinitrate undergoes extensive first-pass metabolism in the liver and is cleared at a rate of 2 to 4 L/minute with a serum half-life of about 1 hour. Isosorbide dinitrate’s clearance is primarily by denitration to the 2-mononitrate (15 to 25%) and the 5-mononitrate (75 to 85%). Both metabolites have biological activity, especially the 5-mononitrate which has an overall half-life of about 5 hours. The 5-mononitrate is cleared by denitration to isosorbide, glucuronidation to the 5-mononitrate glucuronides, and by denitration/hydration to sorbitol. The 2-mononitrate appears to participate in the same metabolic pathways with a half-life of about 2 hours.
Elimination
Hydralazine: Metabolism is the main route for the elimination of hydralazine. Negligible amounts of unchanged hydralazine are excreted in urine.
Isosorbide dinitrate: Most isosorbide dinitrate is eliminated renally as conjugated metabolites.
Specific Populations
No pharmacokinetic studies in special populations were conducted with BiDil. Pharmacokinetics in special populations is based on individual components.
Geriatric Patients -The pharmacokinetics of hydralazine and isosorbide dinitrate, alone or in combination, have not been determined in patients over 65 years of age.
Pediatric Patients - The pharmacokinetics of hydralazine and isosorbide dinitrate, alone or in combination, have not been determined in patients below the age of 18 years.
Gender - There are no studies of gender-dependent effects with hydralazine. In a single dose study with isosorbide dinitrate, no gender-dependent differences in the pharmacokinetics of isosorbide dinitrate and its mononitrate metabolites were found.
Renal Impairment - The effect of renal impairment on the pharmacokinetics of hydralazine has not been determined. In a study with 49 hypertensive patients on chronic therapy with hydralazine in daily doses of 25-200 mg, the daily dose of hydralazine in 19 subjects with severely impaired renal function (creatinine clearance 5-28 mL/min) and in 17 subjects with normal renal function (creatinine clearance >100 mL/min) using a population PK approach was not different, suggesting no need for dose adjustment in patients with renal impairment. The dialyzability of hydralazine has not been determined. In three studies, renal insufficiency did not affect the pharmacokinetics of isosorbide dinitrate. Dialysis is not an effective method for removing isosorbide dinitrate or its metabolite isosorbide-5-mononitrate from the body.
Hepatic Impairment - The effect of hepatic impairment on the pharmacokinetics of hydralazine alone has not been determined. Isosorbide dinitrate concentrations increase in patients with cirrhosis.
Drug-Drug Interactions
No pharmacokinetic drug-drug interaction studies were conducted with BiDil.
Hydralazine: Administration of hydralazine can increase the exposure to a number of drugs including beta-blockers. In healthy males administered a single oral dose of hydralazine 50 mg and propranolol 1 mg/kg, the Cmax and AUC for propranolol approximately doubled. In healthy subjects administered a single oral dose of hydralazine 50 mg and metoprolol 100 mg, the Cmax and AUC for metoprolol increased by 50% and 30%, respectively. In pre-eclamptic women, twice-daily doses of hydralazine 25 mg and metoprolol 50 mg increased the Cmax and AUC for metoprolol by 90% and 40%, respectively.
In healthy males administered single oral doses of hydralazine 25 mg and either lisinopril 20 mg or enalapril 20 mg, Cmax and AUC for lisinopril were each increased 30%, but enalapril concentrations were unaffected.
Intravenous co-administration of 0.2 mg/kg hydralazine HCl and 40 mg furosemide in Japanese patients with congestive heart failure resulted in a 20% increase in the clearance of furosemide.
Isosorbide dinitrate: The vasodilating effects of coadministered isosorbide dinitrate may be additive to those of other vasodilators, including alcohol.
A single dose of 20 mg of isosorbide dinitrate was administered to healthy subjects after pretreatment with 80 mg propranolol three times daily for 48 hours, resulting in no impact on the pharmacokinetics of isosorbide dinitrate and isosorbide-5-mononitrate.
When single 100-mg oral doses of atenolol were administered 2 hours before isosorbide dinitrate at a 10-mg dose no differences in the pharmacokinetics of isosorbide dinitrate or its mononitrates were observed.

13 NONCLINICAL TOXICOLOGY

13.1 Carcinogenesis, Mutagenesis, Impairment of Fertility

Hydralazine hydrochloride: An increased incidence of lung tumors (adenomas and adenocarcinomas) was observed in a lifetime study in Swiss albino mice given hydralazine hydrochloride continuously in their drinking water at a dosage of about 250 mg/kg per day (6 times the MRHD provided by BiDil on a body surface area basis). In a 2-year carcinogenicity study of rats given hydralazine hydrochloride by gavage at dose levels of 15, 30, and 60 mg/kg/day (up to 3 times the MRHD of BiDil on a body surface area basis), microscopic examination of the liver revealed a small, but statistically significant increase in benign neoplastic nodules in males (high-dosage) and females (both high and intermediate dosage groups). Benign interstitial cell tumors of the testes were also significantly increased in the high-dose group.
Hydralazine hydrochloride is mutagenic in bacterial systems, and is positive in rat and rabbit hepatocyte DNA repair studies in vitro. Additional in vivo and in vitro studies using lymphoma cells, germinal cells, fibroblasts from mice, bone marrow cells from Chinese hamsters and fibroblasts from human cell lines did not demonstrate any mutagenic or clastogenic potential for hydralazine hydrochloride.
Isosorbide dinitrate: No long-term animal studies have been performed to evaluate the mutagenic or carcinogenic potential of isosorbide dinitrate. A modified two-litter reproduction study among rats fed isosorbide dinitrate at 25 or 100 mg/kg/day (up to 9 times the Maximum Recommended Human Dose of BiDil on a body surface area basis) revealed no evidence of altered fertility or gestation.

14 CLINICAL STUDIES

BiDil or a combination of isosorbide dinitrate and hydralazine hydrochloride was studied in two placebo-controlled clinical trials in 1,692 patients with mild to severe heart failure (mostly NYHA class II and III) and one active control trial (vs. enalapril) in 804 patients. The results of the trials follow:
Placebo-controlled Study: In the multicenter trial V-HeFT I, the combination of hydralazine and isosorbide dinitrate 75 mg/40 mg 4 times daily (n=186) was compared to placebo (n=273) in men with impaired cardiac function and reduced exercise tolerance (primarily NYHA class II and III) and on therapy with digitalis glycosides and diuretics. There was no overall significant difference in mortality between the two treatment groups. There was, however, a trend favoring hydralazine and isosorbide dinitrate, which on retrospective analysis, was attributable to an effect in blacks (n=128). Survival in white patients (n=324) was similar on placebo and the combination treatment.
Active-controlled Study: In a second study of mortality, V-HeFT II, the combination of hydralazine and isosorbide dinitrate 75 mg/40 mg 4 times daily was compared to enalapril in 804 men with impaired cardiac function and reduced exercise tolerance (NYHA class II and III), and on therapy with digitalis glycosides and diuretics. The combination of hydralazine and isosorbide dinitrate was inferior to enalapril overall, but retrospective analysis showed that the difference was observed in the white population (n=574); there was essentially no difference in the black population (n=215).
Based on these retrospective analyses suggesting an effect on survival in black patients, but showing little evidence of an effect in the white population, a third study was conducted among black patients with heart failure.
Placebo-controlled Study: The A-HeFT trial evaluated BiDil vs. placebo among 1,050 self-identified black patients (over 95% NYHA class III) at 169 centers in the United States. All patients had stable symptomatic heart failure. Patients were required to have LVEF ≤ 35% or left ventricular internal diastolic dimension > 2.9 cm/m^2 plus LVEF < 45%. Patients were maintained on stable background therapy and randomized to BiDil (n=518) or placebo (n=532). BiDil was initiated at 20 mg isosorbide dinitrate/37.5 mg hydralazine hydrochloride three times daily and titrated to a target dose of 40/75 mg three times daily or to the maximum tolerated dose. Patients were treated for up to 18 months.
The randomized population was 60% male, 1% NYHA class II, 95% NYHA class III and 4% NYHA class IV, with a mean age of 57 years, and was generally treated with standard treatments for heart failure including diuretics (94%, almost all loop diuretics), beta-blockers (87%), angiotensin converting enzyme inhibitors (ACE-I; 78%), angiotensin II receptor blockers (ARBs; 28%), either ACE-I or ARB (93%), digitalis glycosides (62%) and aldosterone antagonists (39%).
The primary endpoint was a composite score consisting of all-cause mortality, first hospitalization for heart failure, and responses to the Minnesota Living with Heart Failure questionnaire. The trial was terminated early, at a mean follow-up of 12 months, primarily because of a statistically significant 43% reduction in all-cause mortality in the BiDil-treated group (p=0.012; see Table 2 and Figure 1). The primary endpoint was also statistically in favor of BiDil (p ≤ 0.021). The BiDil-treated group also showed a 39% reduction in the risk of a first hospitalization for heart failure (p<0.001; see Table 2 and Figure 2) and had statistically significant improvement in response to the Minnesota Living with Heart Failure questionnaire, a self-report of the patient’s functional status, at most time points (see Figure 3). Patients in both treatment groups had mean baseline questionnaire scores of 51 (out of a possible 105).
Table 2. Results of A-HeFT (Intent-To-Treat Population)

 | BiDil (N=518) | Placebo (N=532) | Hazard Ratio (95% CI) | P
Composite | -0.16±1.93 | -0.47±2.04 | — | 0.021
All-cause mortality | 6.2% | 10.2% | 0.57 (0.37, 0.89) | 0.012
Hospitalization for heart failure | 16.4% | 24.4% | 0.61 (0.46, 0.80) | <0.001

Effects on survival and hospitalization for heart failure were similar in subgroups by age, gender, baseline disease, and use of concomitant medications, as shown in Figure 4.

Patients treated with BiDil in the A-HeFT study had randomly measured blood pressures on average 3/3 mmHg lower than did patients on placebo. The contribution of the difference in blood pressure to the overall outcome difference is unknown. Whether both hydralazine and isosorbide dinitrate contribute to the overall outcome difference has not been studied in outcome trials. Isosorbide dinitrate and hydralazine have not been systematically studied for the treatment of heart failure as separate agents, and neither drug is indicated for heart failure.

16 HOW SUPPLIED/STORAGE AND HANDLING

BiDil Tablets contain 20 mg of isosorbide dinitrate and 37.5 mg of hydralazine hydrochloride. They are biconvex, approximately 8 mm in diameter, scored, film-coated, orange tablets debossed "20" on one side over the score and "N" on the other side.

- NDC 24338-010-09: Bottles of 90

Store at 25°C (77°F), excursions permitted to 15-30°C (59-86°F). [See USP Controlled Room Temperature.] Keep bottles tightly closed.
Protect from light. Dispense in a light-resistant, tight container.

17 PATIENT COUNSELING INFORMATION

Patients should be informed of possible side effects and advised to take the medication regularly and continuously as directed.
Headache
Inform patients that headaches often accompany treatment with BiDil, especially during initiation of treatment. Advise patients to consult a physician to adjust the dose of BiDil if headache continues with repeated dosing.
Hypotension
Warn patients about lightheadedness on standing.
Advise patients that inadequate fluid intake or excessive fluid loss from perspiration, diarrhea or vomiting may lead to an excessive fall in blood pressure and cause lightheadedness or even syncope. If syncope does occur, advise patients to discontinue BiDil and notify their prescribing physician as soon as possible.
Phosphodiesterase-5 Inhibitors
Advise patients to inform their physicians if they are taking, or planning to take, sildenafil, vardenafil, or tadalafil. Bidil should not be taken concomitantly with phosphodiesterase-5 inhibitors.
Worsening Ischemic Heart Disease
Advise patients to inform their physicians of any worsening of symptoms of myocardial ischemia, especially those with hypertrophic cardiomyopathy.
Systemic Lupus Erythematosus-like Symptoms
Advise patients if symptoms suggestive of systemic lupus erythematosus—such as arthralgia, fever, chest pain, prolonged malaise—occur to notify their prescribing physician.
Peripheral Neuritis
Advise patients if symptoms of peripheral neuritis—paresthesia, numbness, and tingling—occur to notify the prescribing physician.
Manufactured for:

Azurity Pharmaceuticals, Inc.
Woburn, MA 01801 USA
Manufactured by:
Lannett Company, Inc.
Philadelphia, PA 19136
BiDil is a registered trademark of Azurity Pharmaceuticals, Inc.
© 2025
All rights reserved

BDL-PI-07

CIA75474J

PRINCIPAL DISPLAY PANEL - 90 Tablet Bottle Label

NDC 24338-010-09
90 tablets

BiDil®
isosorbide dinitrate and hydralazine HCl tablets

20 mg/37.5 mg

Store at room temperature 15°C - 30°C (59°F - 86°F)

BDL-TL-09-01 Rev. 11/25
CIB71996C

Rx only